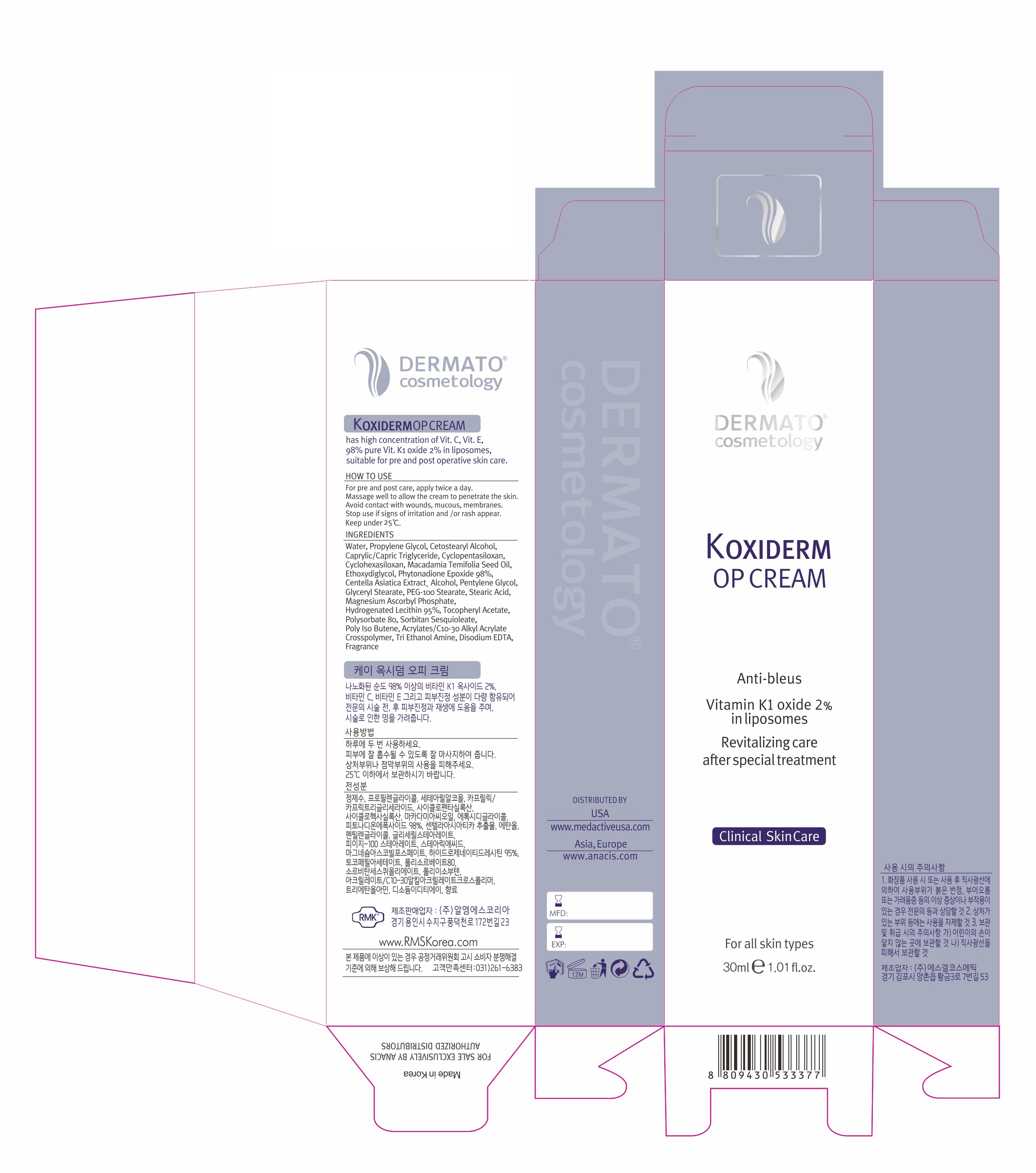 DRUG LABEL: K Oxiderm OP Post Procedure skin care bruise
NDC: 71588-0011 | Form: CREAM
Manufacturer: EZEKIELCOSMETIC CO., LTD
Category: otc | Type: HUMAN OTC DRUG LABEL
Date: 20170825

ACTIVE INGREDIENTS: MAGNESIUM ASCORBYL PHOSPHATE 0.5 g/100 mL
INACTIVE INGREDIENTS: WATER; ALCOHOL; MAGNESIUM PHOSPHIDE

Drug Facts

ACTIVE INGREDIENT

Magnesium Ascorbyl Phosphate

INACTIVE INGREDIENT

water, propylene glycol, alcohol etc

PURPOSE

Reduces Discoloration on skin

keep out of reach of the children

INDICATIONS AND USAGE

for 4~5 days before cosmetic application, apply thinly twice a day, morning and night, after cleansing the skin

apply K oxiderm OP cream right after cosmetic application

K oxiderm OP cream is recommended for 10 to 15 days as preparatory skin care before and after surgical and medical cosmetic procedure

WARNINGS

1. If the following symptoms occur after product use, stop using the product immediately and consult a dermatologist (continuous use can exacerbate the symptoms).
1) Occurrence of red spots, swelling, itchiness, and other skin irritation
2) If the symptoms above occur after the application area is exposed to direct sunlight
2. Do not use on open wounds, eczema, and other skin irritations
3. Precaution for Storage and Handling
1) Close the lid after use
2) Keep out of reach of infants and children
3) Do not to store in a place with high/low temperature and exposed to direct sunlight

4. Use as avoiding eye areas.

DOSAGE AND ADMINISTRATION

for external use only